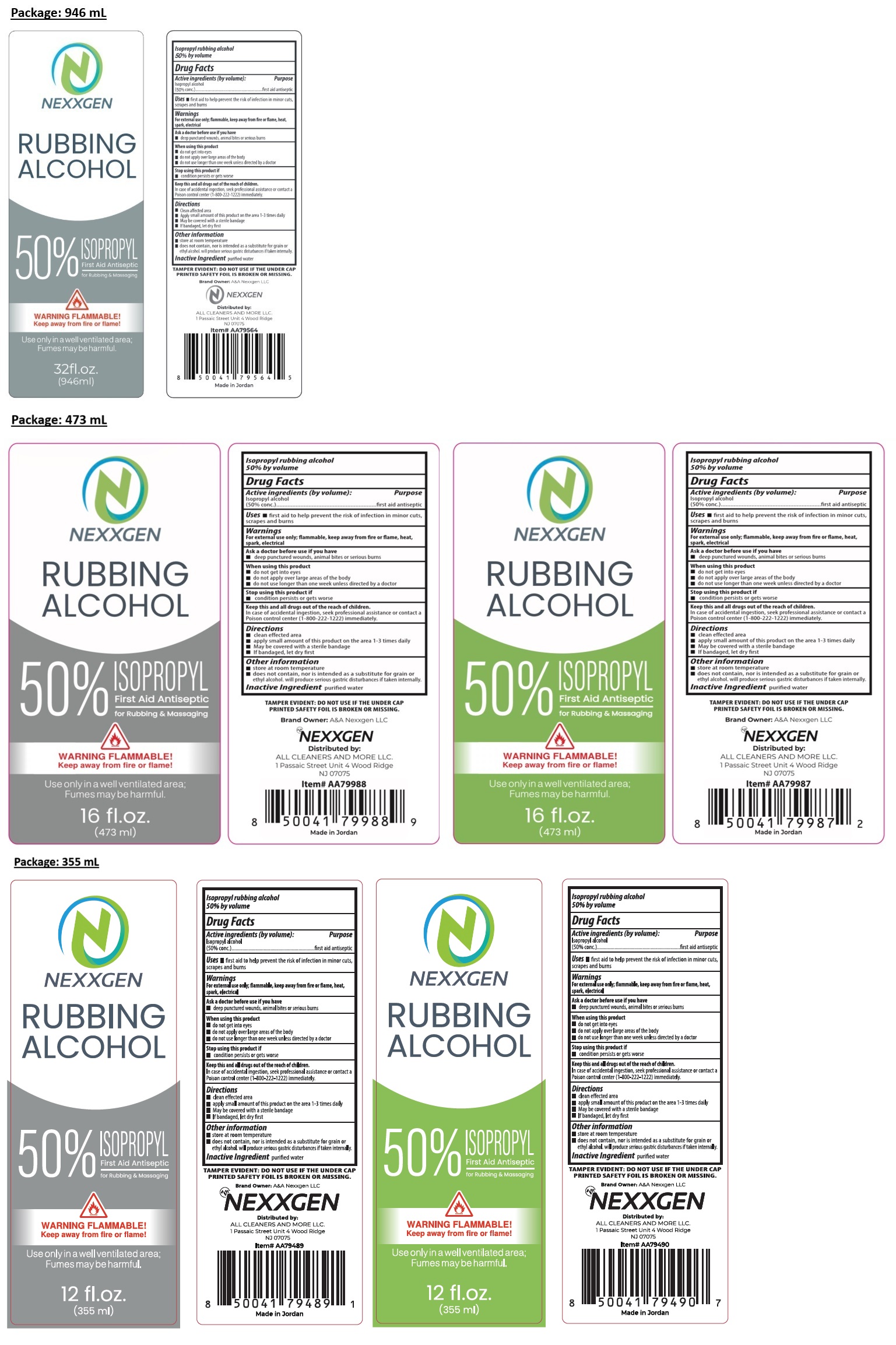 DRUG LABEL: NEXXGEN 50% RUBBING ALCOHOL
NDC: 83629-019 | Form: LIQUID
Manufacturer: A & A Nexxgen LLC
Category: otc | Type: HUMAN OTC DRUG LABEL
Date: 20260116

ACTIVE INGREDIENTS: ISOPROPYL ALCOHOL 50 mL/100 mL
INACTIVE INGREDIENTS: WATER

NEXXGEN RUBBING ALCOHOL

Active ingredients (by volume):

Isopropyl alcohol (50% conc.)

Purpose

first aid antiseptic

Uses

• first aid to help prevent the risk of infection in minor cuts, scrapes and burns

Warnings

For external use only; flammable, keep away from fire or flame, heat, spark, electrical

Ask a doctor before use if you have
• deep punctured wounds, animal bites or serious burns

When using this product
• do not get into eyes
• do not apply over large areas of the body
• do not use longer than one week unless directed by a doctor

Stop using this product if
• condition persists or gets worse

KEEP OUT OF REACH OF CHILDREN

Keep this and all drugs out of the reach of children.
In case of accidental ingestion, seek professional assistance or contact a Poison control center (1‑800‑222‑1222) immediately.

Directions

• Clean affected area
• Apply small amount of this product on the area 1-3 times daily
• May be covered with a sterile bandage
• If bandaged, let dry first

Other information

• store at room temperature
• does not contain, nor is intended as a substitute for grain or ethyl alcohol. Will produce serious gastric disturbances if taken internally.

Inactive Ingredient

purified water

for Rubbing & Massaging

Use only in a well ventilated area; Fumes may be harmful.

TAMPER EVIDENT: DO NOT USE IF THE UNDER CAP PRINTED SAFETY FOIL IS BROKEN OR MISSING.

Brand Owner: A&A Nexxgen LLC

Distributed by:
ALL CLEANERS AND MORE LLC.
1 Passaic Street Unit 4 Wood Ridge
NJ 07075

Made in Jordan